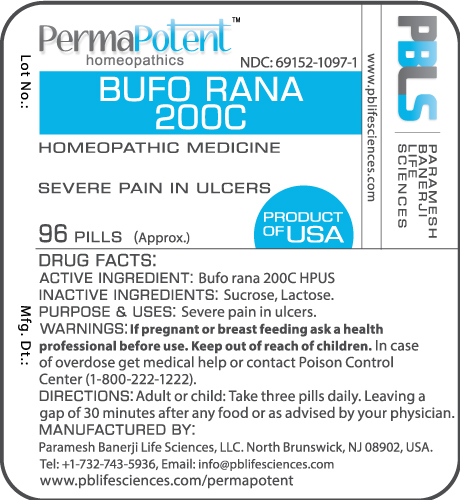 DRUG LABEL: Bufo rana 200C
NDC: 69152-1097 | Form: PELLET
Manufacturer: Paramesh Banerji Life Sciences LLC
Category: homeopathic | Type: HUMAN OTC DRUG LABEL
Date: 20170202

ACTIVE INGREDIENTS: BUFO BUFO CUTANEOUS GLAND 200 [hp_C]/1 1
INACTIVE INGREDIENTS: SUCROSE; LACTOSE, UNSPECIFIED FORM

DRUG FACTS: Active Ingredient

Bufo rana 200C HPUS

Inactive Ingredients

Sucrose, Lactose

Purpose

Severe pain in ulcers

Uses

Severe pain in ulcers

Warnings

If pregnant or breast feeding ask a health professional before use.

Keep out of reach of children. In case of overdose get medical help or contact Poison Control Center (1-800-222-1222).

Direction

Adult or child: Take three pills daily. Leaving a gap of 30 minutes after any food or as advised by your physician.

Manufactured by

Paramesh Banerji Life Sciences, LLC.

North Brunswick, NJ 08902, USA.

Tel: +1-732-743-5936,

Email: info@pblifesciences.com

www.pblifesciences.com/permapotent

Principal Display Panel

NDC: 69152-1097-1

Bufo rana 200C

Homeopathic Medicine

Severe pain in ulcers

96 Pills (Approx.)

Product of USA